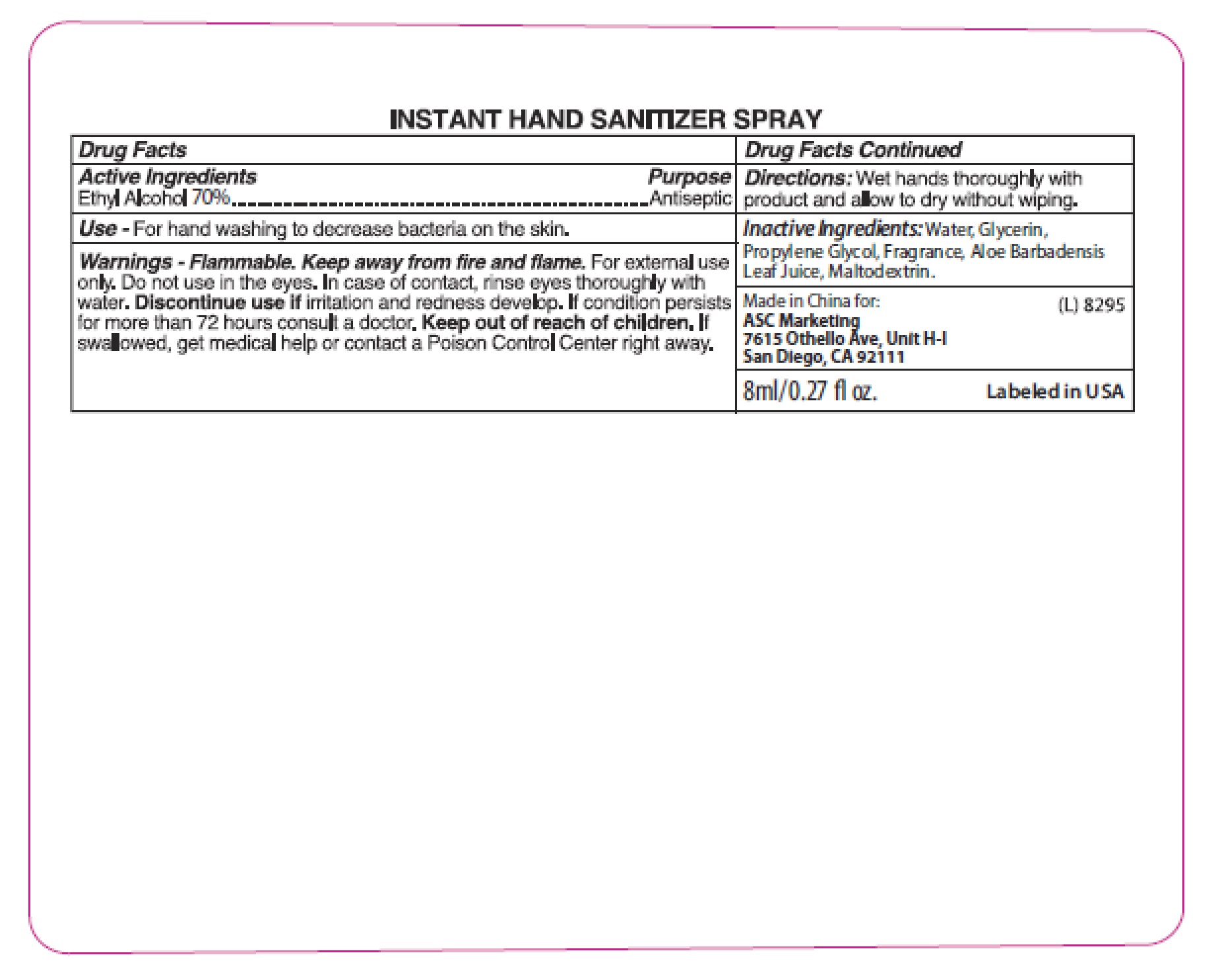 DRUG LABEL: ANTIBACTERIAL HAND SANITIZER
NDC: 73145-009 | Form: GEL
Manufacturer: ASC Marketing Ltd.
Category: otc | Type: HUMAN OTC DRUG LABEL
Date: 20250407

ACTIVE INGREDIENTS: ALCOHOL 70 mL/100 mL
INACTIVE INGREDIENTS: WATER; ALOE VERA LEAF; GLYCERIN; PROPYLENE GLYCOL; MALTODEXTRIN

73145-009, ASC ANTIBACTERIAL HAND SANITIZER

Active ingredient

Ethyl alcohol 70%

Purpose

Antiseptic

Uses

For handwashing to decrease bacteria on the skin.

Warnings

Flammable. Keep away from fire and flame. For external use only. Do not use in eyes. In case of contact，rinse eyes thoroughly with water. Discontinue use if irritation or redness develop. If condition persists for more than 72 hours consult a doctor.

Keep out of reach of children

If swallowed, get medical help or contact a Poison Control Centre right away.

Directions

Wet hands thoroughly for with product and allow to dry without wiping.

Inactive Ingredients

Water, Glycerin, Propylene Glycol, Fragrance, Aloe Barbadensis Leaf Juice, Maltodextrin.